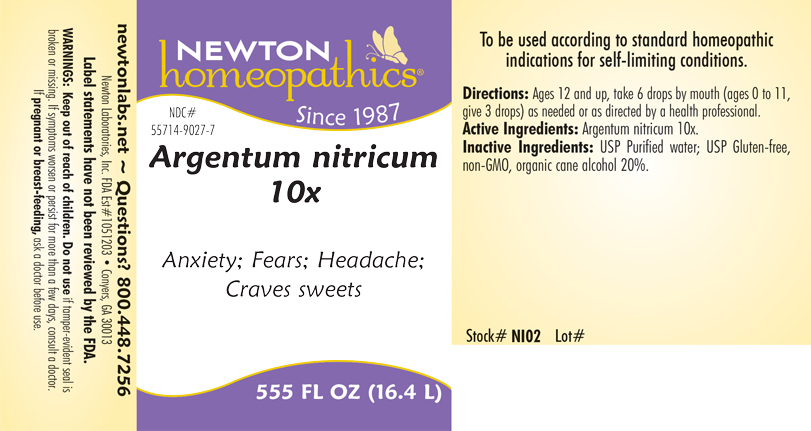 DRUG LABEL: Argentum nitricum
NDC: 55714-9027 | Form: LIQUID
Manufacturer: Newton Laboratories, Inc.
Category: homeopathic | Type: HUMAN OTC DRUG LABEL
Date: 20240625

ACTIVE INGREDIENTS: SILVER NITRITE 10 [hp_X]/1 L
INACTIVE INGREDIENTS: WATER; ALCOHOL

ArgentumNi 9027L

INDICATIONS & USAGE SECTION

Anxiety; Fears; Headache; Craves sweets

DOSAGE & ADMINISTRATION SECTION

Directions: Ages 12 and up, take 6 drops by mouth, (ages 0 to 11, give 3 drops) as needed or as directed by a health professional.

OTC - ACTIVE INGREDIENT SECTION

Argentum nitricum 10x

OTC - PURPOSE SECTION

Anxiety; Fears; Headache; Craves sweets

INACTIVE INGREDIENT SECTION

Inactive Ingredients: USP Purified Water; USP Gluten-free, non-GMO, organic cane alcohol 20%.

QUESTIONS SECTION

newtonlabs.net – Questions? 800.448.7256

Newton Laboratories, Inc. FDA Est # 1051203 - Conyers, GA 30013

WARNINGS SECTION

Warning: Keep out of reach of children. Do not use if tamper - evident seal is broken or missing. If symptoms worsen or persist for more than a few days, consult a doctor. If pregnant or breast-feeding, ask a doctor before use.

OTC - PREGNANCY OR BREAST FEEDING SECTION

If pregnant or breast-feeding, ask a doctor before use.

OTC - KEEP OUT OF REACH OF CHILDREN SECTION

Keep out of reach of children.